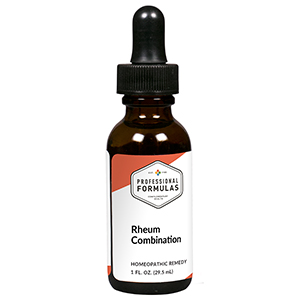 DRUG LABEL: Rheum Combination
NDC: 63083-9240 | Form: LIQUID
Manufacturer: Professional Complementary Health Formulas
Category: homeopathic | Type: HUMAN OTC DRUG LABEL
Date: 20190815

ACTIVE INGREDIENTS: STAR ANISE 1 [hp_X]/29.5 mL; VERONICASTRUM VIRGINICUM WHOLE 1 [hp_X]/29.5 mL; MEDICAGO SATIVA WHOLE 1 [hp_X]/29.5 mL; RHEUM OFFICINALE STEM 1 [hp_X]/29.5 mL; SENNA LEAF 1 [hp_X]/29.5 mL; FRANGULA ALNUS BARK 2 [hp_X]/29.5 mL; ALOE 4 [hp_X]/29.5 mL; BRYONIA ALBA ROOT 4 [hp_X]/29.5 mL; STRYCHNOS NUX-VOMICA SEED 4 [hp_X]/29.5 mL; CITRULLUS COLOCYNTHIS FRUIT PULP 6 [hp_X]/29.5 mL; GRAPHITE 8 [hp_X]/29.5 mL
INACTIVE INGREDIENTS: ALCOHOL; WATER

R240

ACTIVE INGREDIENTS

Illicium anisatum 1X
Leptandra virginica 1X
Medicago sativa 1X
Rheum officinale 1X
Senna 1X
Rhamnus frangula 2X
Aloe socotrina 4X
Bryonia 4X
Nux vomica 4X
Colocynthis 6X
Graphites 8X

QUESTIONS

Professional Formulas

PO Box 2034 Lake Oswego, OR 97035

INDICATIONS

For the temporary relief of constipation, flatulence, or intestinal cramps.*

PURPOSE

*Claims based on traditional homeopathic practice, not accepted medical evidence. Not FDA evaluated.

WARNINGS

Do not use for more than 30 days. This remedy may act as a mild laxative.* Do not use if pregnant or in cases of severe intestinal spasms. Keep out of the reach of children. In case of overdose, get medical help or contact a poison control center right away.

Keep out of the reach of children.

PREGNANCY OR BREAST FEEDING

If pregnant or breastfeeding, ask a healthcare professional before use.

DIRECTIONS

Place drops under tongue 30 minutes before/after meals. Adults and children 12 years and over: Take 10 drops up to 3 times per day. Consult a physician for use in children under 12 years of age.

OTHER INFORMATION

Tamper resistant. If seal is broken, do not use. After opening, close container tightly and store at room temperature away from heat.

INACTIVE INGREDIENTS

40% ethanol, purified water.

LABEL

Est 1985

Professional Formulas

Complementary Health

Rheum Combination

Homeopathic Remedy

1 FL. OZ. (29.5 mL)